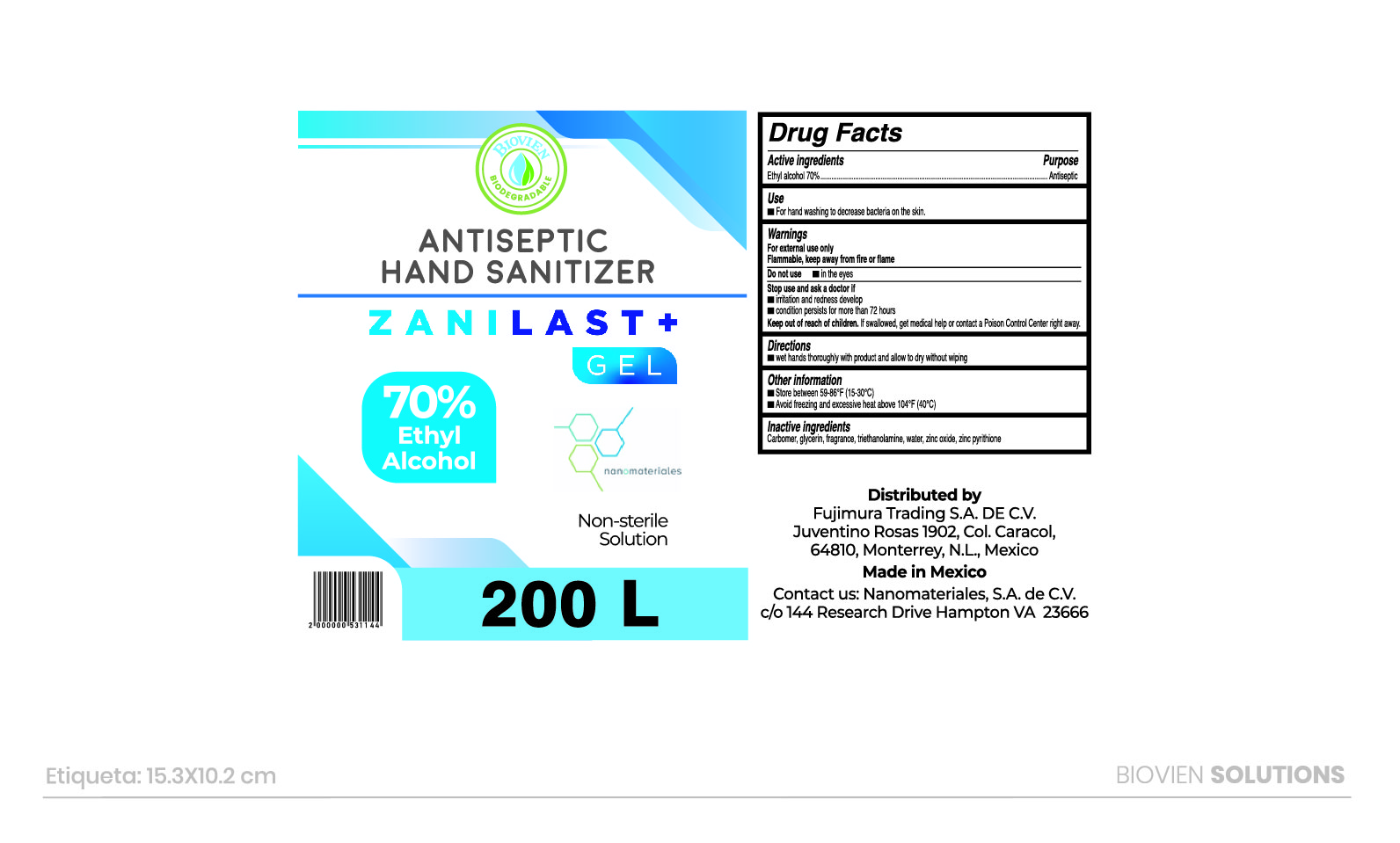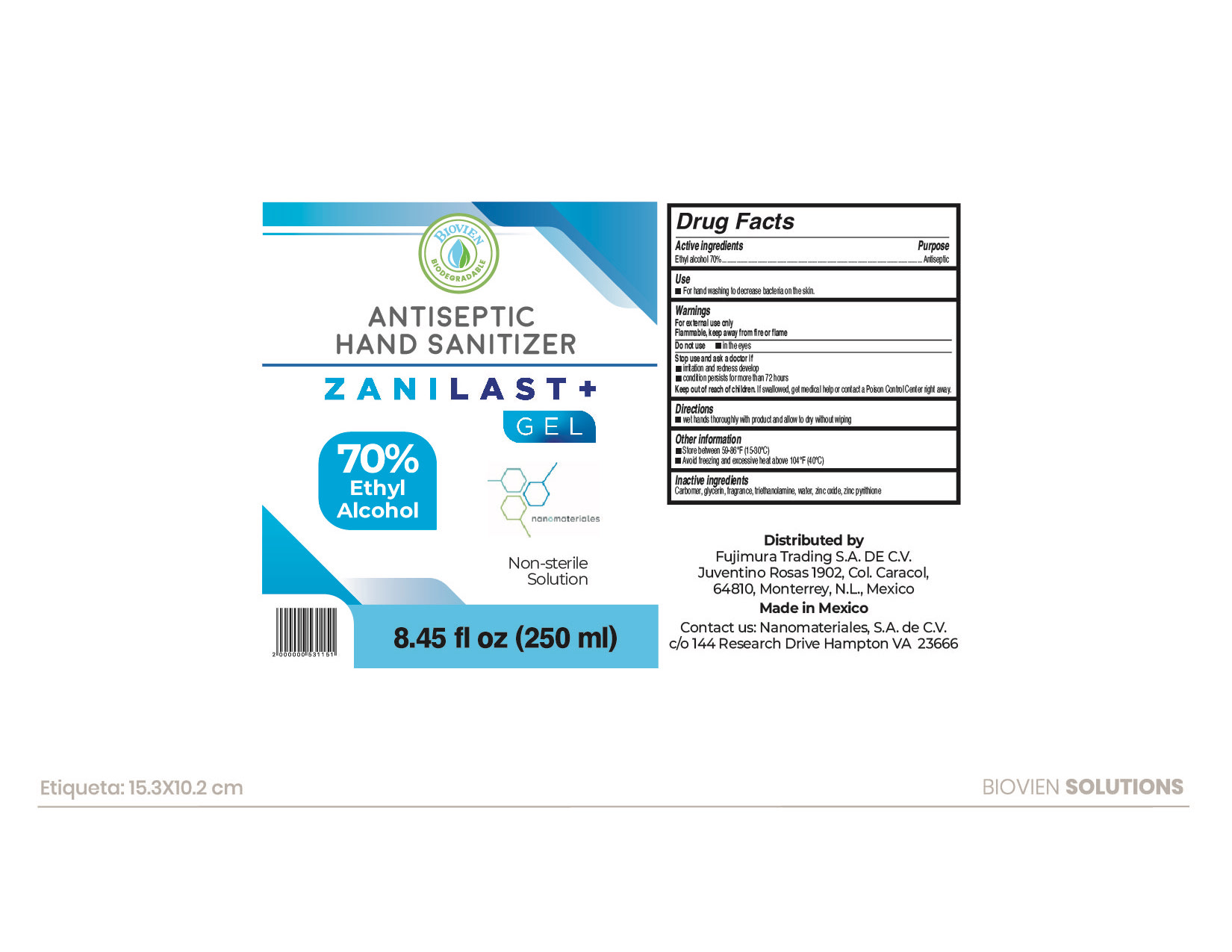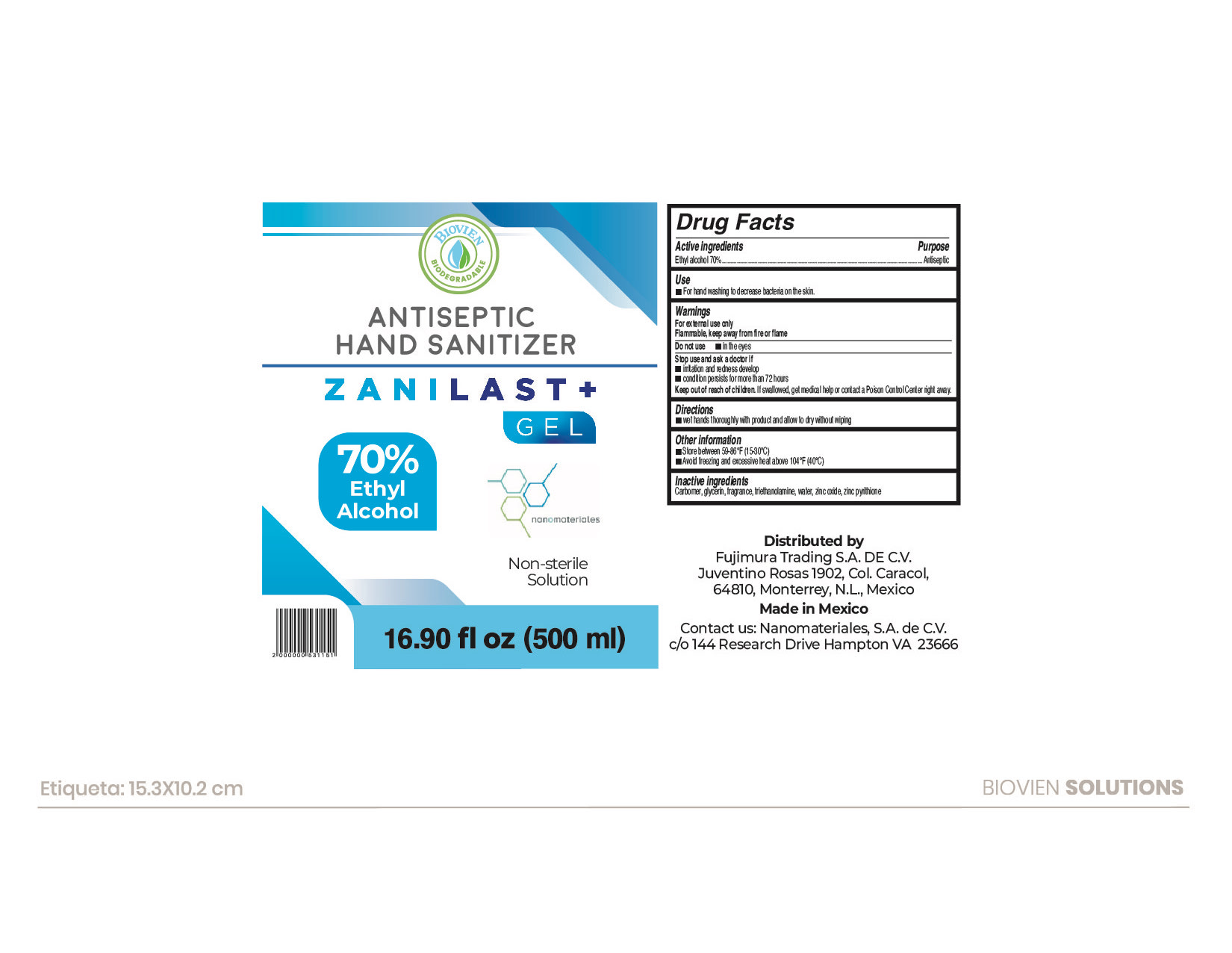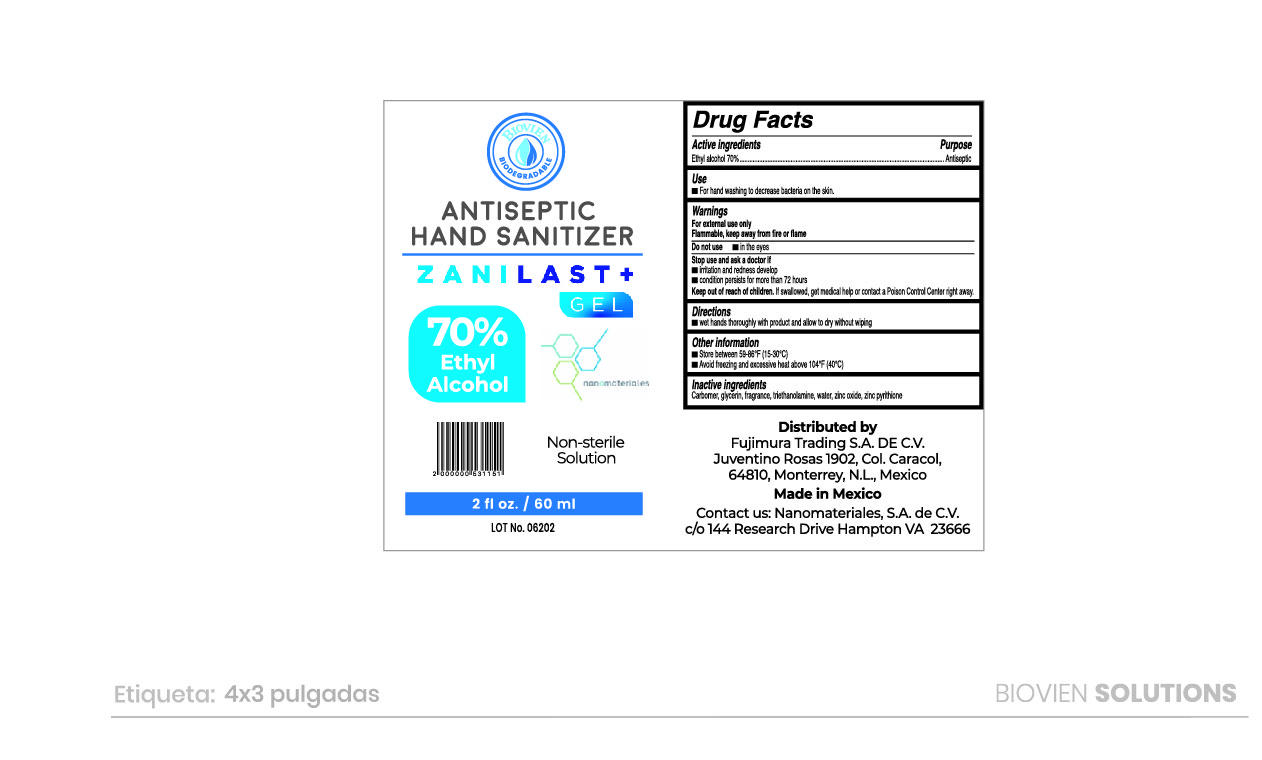 DRUG LABEL: Hand Sanitizer
NDC: 69912-009 | Form: GEL
Manufacturer: Nanomateriales, S.A. de C.V.
Category: otc | Type: HUMAN OTC DRUG LABEL
Date: 20200710

ACTIVE INGREDIENTS: ALCOHOL 70 mL/100 mL
INACTIVE INGREDIENTS: ZINC OXIDE; CARBOMER 940; GLYCERIN; LIMONENE, (+)-; WATER; TROLAMINE; PYRITHIONE ZINC

ZANILAST+ GEL 70% ALCOHOL

Active Ingredients

Ethyl Alcohol 70%

Purpose: Antiseptic

Use

For hand washing to decrease bacteria on the skin.

Warnings

For external use only. Flammable. Keep away from heat or flame

Do not use

- in the eyes

Stop use and ask a doctor if irritation and redness develop. Condition persists for more than 72 hours.

Keep out of reach of children. If swallowed, get medical help or contact a Poison Control Center right away.

Directions

- Wet hands thoroughly with product and allow to dry without wiping

Other information

- Store between 59-86ºF (15-30ºC)
- Avoid freezing and excessive heat above (40ºC) 104ºF

Inactive ingredients

Carbomer, glycerin, fragrance, triethanolamine, water, zinc oxide, zinc pyrithione

PACKAGE LABEL

200000 mL NDC 69912-009-06

60 mL NDC 69912-009-05

500 mL NDC 69912-009-03

250 mL NDC 69912-009-04